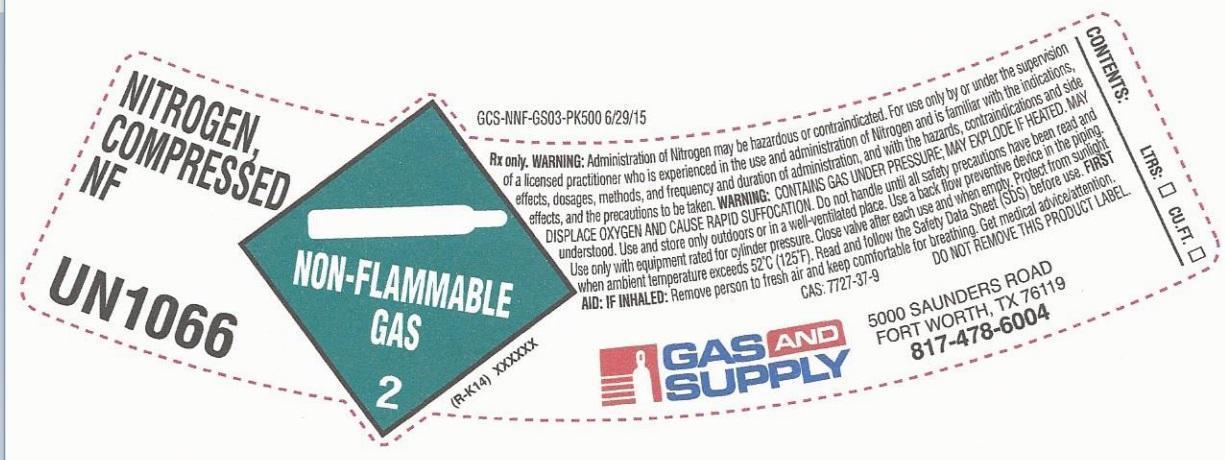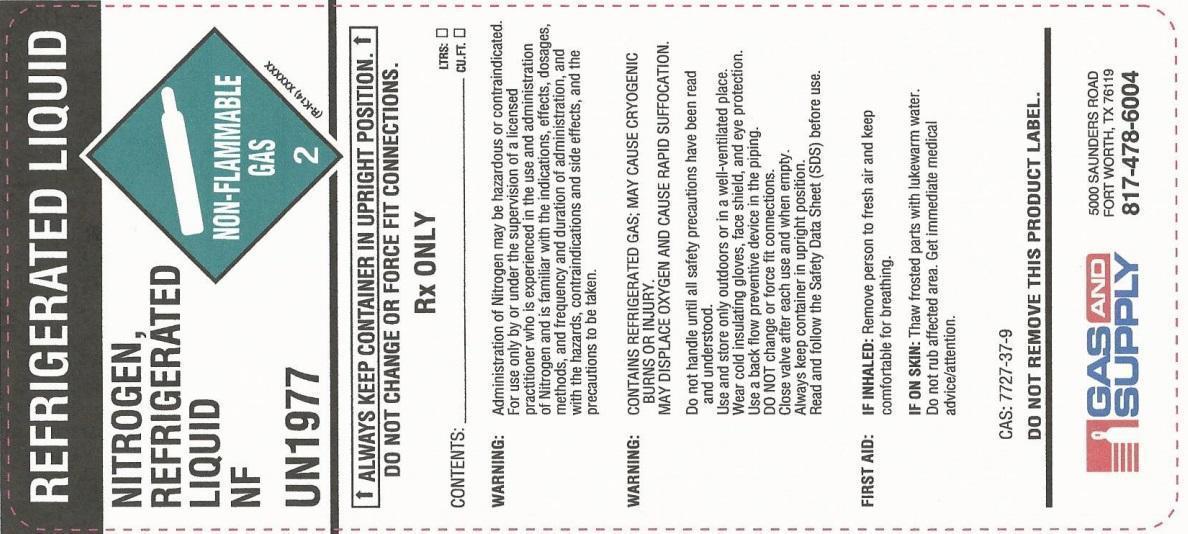 DRUG LABEL: Nitrogen
NDC: 70101-012 | Form: GAS
Manufacturer: Gas and Supply
Category: animal | Type: PRESCRIPTION ANIMAL DRUG LABEL
Date: 20251203

ACTIVE INGREDIENTS: NITROGEN 995 mL/1 L

PACKAGE LABEL

NITROGEN, COMPRESSED NF
UN1066
NON-FLAMMABLE GAS 2
Rx only. WARNING: Administration of Nitrogen may be hazardous or contraindicated. For use only by or under the supervision of a licensed practitioner who is experienced in the use and administration of Nitrogen and is familiar with the indications, effects, dosages, methods, and frequency and duration of administration, and with the hazards, contraindications and side effects, and the precautions to be taken. WARNING: CONTAINS GAS UNDER PRESSURE; MAY EXPLODE IF HEATED. MAY DISPLACE OXYGEN AND CAUSE RAPID SUFFOCATION. Do not handle until all safety precautions have been read and understood. Use and store only outdoors or in a well-ventilated place. Use a back flow preventive device in the piping. Use only with equipment rated for cylinder pressure. Close valve after each use and when empty. Protect from sunlight when ambient temperature exceeds 52 degrees C (125 degrees F). Read and follow the Safety Data Sheet (SDS) before use. FIRST AID: IF INHALED: Remove person to fresh air and keep comfortable for breathing. Get medical advice/attention.
CAS: 7727-37-9 DO NOT REMOVE THIS PRODUCT LABEL.
CONTENTS: LTRS. CU.FT.
GAS AND SUPPLY
5000 SAUNDERS ROAD
FORT WORTH, TX 76119
817-478-6004

PACKAGE LABEL

NITROGEN, REFRIGERATED LIQUID NF
UN1977
NON-FLAMMABLE GAS 2
ALWAYS KEEP CONTAINER IN UPRIGHT POSITION.
DO NOT CHANGE OR FORCE FIT CONNECTIONS.
Rx ONLY
CONTENTS: LTRS. CU.FT.
WARNING: Administration of Nitrogen may be hazardous or contraindicated. For use only by or under the supervision of a licensed practitioner who is experienced in the use and administration of Nitrogen and is familiar with the indications, effects, dosages, methods, and frequency and duration of administration, and with the hazards, contraindications and side effects, and the precautions to be taken.
WARNING: CONTAINS REFRIGERATED GAS; MAY CAUSE CRYOGENIC BURNS OR INJURY.
MAY DISPLACE OXYGEN AND CAUSE RAPID SUFFOCATION.
Do not handle until all safety precautions have been read and understood. Use and store only outdoors or in well-ventilated place. Wear cold insulating gloves, face shield, and eye protection. Use a back flow preventive device in the piping. DO NOT change or force fit connections. Close valve after each use and when empty. Always keep container in upright position. Read and follow the Safety Data Sheet (SDS) before use.
FIRST AID: IF INHALED: Remove person to fresh air and keep comfortable for breathing. IF ON SKIN: Thaw frosted parts with lukewarm water. Do not rub affected area. Get immediate medical advice/attention.
CAS: 7727-37-9
DO NOT REMOVE THIS PRODUCT LABEL.
GAS AND SUPPLY
5000 SAUNDERS ROAD
FORT WORTH, TX 76119
817-478-6004